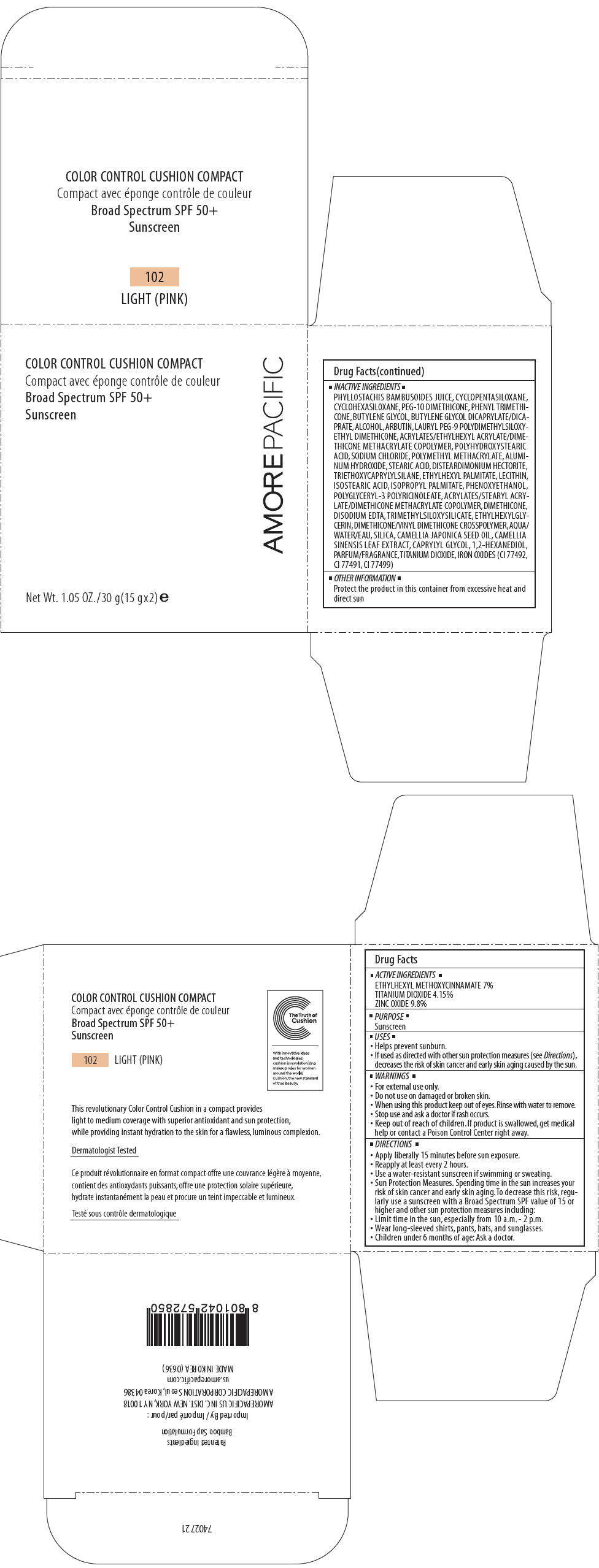 DRUG LABEL: AMOREPACIFIC COLOR CONTROL CUSHION COMPACT NO.102
NDC: 43419-528 | Form: LOTION
Manufacturer: AMOREPACIFIC CORPORATION
Category: otc | Type: HUMAN OTC DRUG LABEL
Date: 20241008

ACTIVE INGREDIENTS: ZINC OXIDE 2.94 g/30 g; OCTINOXATE 2.1 g/30 g; TITANIUM DIOXIDE 1.245 g/30 g
INACTIVE INGREDIENTS: POLYGLYCERYL-3 RICINOLEATE; TRIMETHYLSILOXYSILICATE (M/Q 0.6-0.8); PHYLLOSTACHYS RETICULATA RESIN; CYCLOMETHICONE 5; CYCLOMETHICONE 6; PHENYL TRIMETHICONE; PEG-10 DIMETHICONE (600 CST); BUTYLENE GLYCOL; BUTYLENE GLYCOL DICAPRYLATE/DICAPRATE; ALCOHOL; LAURYL PEG-9 POLYDIMETHYLSILOXYETHYL DIMETHICONE; POLY(METHYL METHACRYLATE; 450000 MW); SODIUM CHLORIDE; FERRIC OXIDE YELLOW; ALUMINUM HYDROXIDE; DISTEARDIMONIUM HECTORITE; STEARIC ACID; PHENOXYETHANOL; TRIETHOXYCAPRYLYLSILANE; ETHYLHEXYL PALMITATE; ISOSTEARIC ACID; ISOPROPYL PALMITATE; FERRIC OXIDE RED; DIMETHICONE; ETHYLHEXYLGLYCERIN; EDETATE DISODIUM ANHYDROUS; FERROSOFERRIC OXIDE; WATER; GREEN TEA LEAF; CAPRYLYL GLYCOL; 1,2-HEXANEDIOL; POLYHYDROXYSTEARIC ACID (2300 MW); TOCOPHEROL; DIMETHICONE/VINYL DIMETHICONE CROSSPOLYMER (SOFT PARTICLE)

AMOREPACIFIC COLOR CONTROL CUSHION COMPACT NO.102

Drug Facts

ACTIVE INGREDIENTS

ETHYLHEXYL METHOXYCINNAMATE 7%

TITANIUM DIOXIDE 4.15%

ZINC OXIDE 9.8%

PURPOSE

Sunscreen

USES

- Helps prevent sunburn.
- If used as directed with other sun protection measures (see Directions), decreases the risk of skin cancer and early skin aging caused by the sun.

WARNINGS

- For external use only.

- Do not use on damaged or broken skin.

- When using this product keep out of eyes. Rinse with water to remove.

- Stop use and ask a doctor if rash occurs.

- Keep out of reach of children. If product is swallowed, get medical help or contact a Poison Control Center right away.

DIRECTIONS

- Apply liberally 15 minutes before sun exposure.
- Reapply at least every 2 hours.
- Use a water-resistant sunscreen if swimming or sweating.
- Sun Protection Measures. Spending time in the sun increases your risk of skin cancer and early skin aging. To decrease this risk, regularly use a sunscreen with a Broad Spectrum SPF value of 15 or higher and other sun protection measures including:
  - Limit time in the sun, especially from 10 a.m. - 2 p.m.
  - Wear long-sleeved shirts, pants, hats, and sunglasses.
- Children under 6 months of age: Ask a doctor.

INACTIVE INGREDIENTS

PHYLLOSTACHIS BAMBUSOIDES JUICE, CYCLOPENTASILOXANE, CYCLOHEXASILOXANE, PEG-10 DIMETHICONE, PHENYL TRIMETHICONE, BUTYLENE GLYCOL, BUTYLENE GLYCOL DICAPRYLATE/DICAPRATE, ALCOHOL, ARBUTIN, LAURYL PEG-9 POLYDIMETHYLSILOXYETHYL DIMETHICONE, ACRYLATES/ETHYLHEXYL ACRYLATE/DIMETHICONE METHACRYLATE COPOLYMER, POLYHYDROXYSTEARIC ACID, SODIUM CHLORIDE, POLYMETHYL METHACRYLATE, ALUMINUM HYDROXIDE, STEARIC ACID, DISTEARDIMONIUM HECTORITE, TRIETHOXYCAPRYLYLSILANE, ETHYLHEXYL PALMITATE, LECITHIN, ISOSTEARIC ACID, ISOPROPYL PALMITATE, PHENOXYETHANOL, POLYGLYCERYL-3 POLYRICINOLEATE, ACRYLATES/STEARYL ACRYLATE/DIMETHICONE METHACRYLATE COPOLYMER, DIMETHICONE, DISODIUM EDTA, TRIMETHYLSILOXYSILICATE, ETHYLHEXYLGLYCERIN, DIMETHICONE/VINYL DIMETHICONE CROSSPOLYMER, AQUA/WATER/EAU, SILICA, CAMELLIA JAPONICA SEED OIL, CAMELLIA SINENSIS LEAF EXTRACT, CAPRYLYL GLYCOL, 1,2-HEXANEDIOL, PARFUM/FRAGRANCE, TITANIUM DIOXIDE, IRON OXIDES (CI 77492, CI 77491, CI 77499)

OTHER INFORMATION

Protect the product in this container from excessive heat and direct sun

Questions?

support@us.amorepacific.com

PRINCIPAL DISPLAY PANEL - 30 g (15 g x 2) Container Carton

COLOR CONTROL CUSHION COMPACT

Broad Spectrum SPF 50+
Sunscreen

AMOREPACIFIC

Net Wt. 1.05 OZ./30 g(15 gx2) e